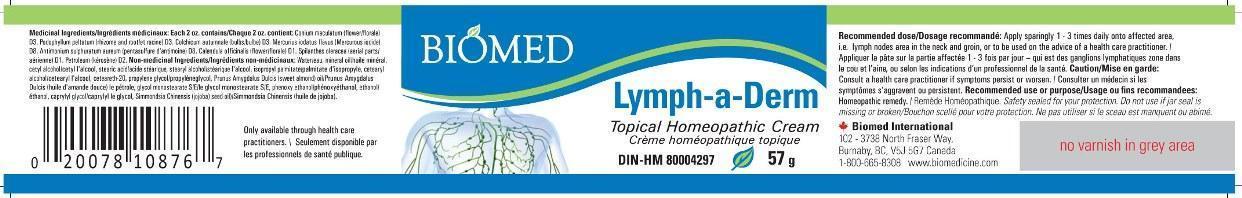 DRUG LABEL: Lymph-A-Derm
NDC: 57518-0001 | Form: CREAM
Manufacturer: Biomed International
Category: homeopathic | Type: HUMAN OTC DRUG LABEL
Date: 20140808

ACTIVE INGREDIENTS: CALENDULA OFFICINALIS FLOWERING TOP 1 [hp_X]/1 g; ACMELLA OLERACEA FLOWERING TOP 1 [hp_X]/1 g; PETROLATUM 2 [hp_X]/1 g; COLCHICUM AUTUMNALE BULB 3 [hp_X]/1 g; CONIUM MACULATUM FLOWERING TOP 3 [hp_X]/1 g; PODOPHYLLUM 3 [hp_X]/1 g; ANTIMONY PENTASULFIDE 8 [hp_X]/1 g; MERCUROUS IODIDE 8 [hp_X]/1 g
INACTIVE INGREDIENTS: CAPRYLYL GLYCOL; POLYOXYL 20 CETOSTEARYL ETHER; CETOSTEARYL ALCOHOL; CETYL ALCOHOL; GLYCOL STEARATE; ISOPROPYL PALMITATE; MINERAL OIL; PHENOXYETHANOL; PROPYLENE GLYCOL; ALMOND OIL; JOJOBA OIL; STEARIC ACID; STEARYL ALCOHOL; WATER

Drug Facts:

ACTIVE INGREDIENTS:

Calendula officinalis 1X, Spilathes oleracea 1X, Petroleum 2X, Colchicum autumnale 3X, Conium maculatum 3X, Podophyllum peltatum 3X, Antimonium sulphuratum aureum 8X, Mercurius iodatus flavus 8X.

PURPOSE:

Homeopathic remedy.

WARNINGS:

Safety sealed for your protection.

Do not use if jar seal is missing or broken.

RECOMMENDED DOSE:

Apply sparingly 1-3 times daily onto affected area, i.e. lymph nodes area in the neck and groin, or to be used on the adivice of a healh care practitioner.

PURPOSE:

Homeopathic remedy.

INACTIVE INGREDIENTS:

Caprylyl glycol, Ceterarth 20, Cetearyl alcohol, Cetyl alcohol, Glycol monostearate S/E, Isopropyl palmitate, Mineral oil, Phenoxyethanol, Propylene glycol, Prunus amygdalus dulcis (Sweet Almond) oil, Simmondsia chinensis (Jojoba) seed oil, Stearic acid, Stearyl alcohol, Water.

QUESTIONS:

Biomed International

102-3738 North Fraser Way,

Burnaby, BC V5J 5G7 Canada

1-800-665-8308 www.biomedicine.com

PACKAGE LABEL DISPLAY:

BIOMED

Lymph-a-Derm

Topical Homeopathic Cream

Crème homéopathique topique

DIN-HM 80004297

57 g